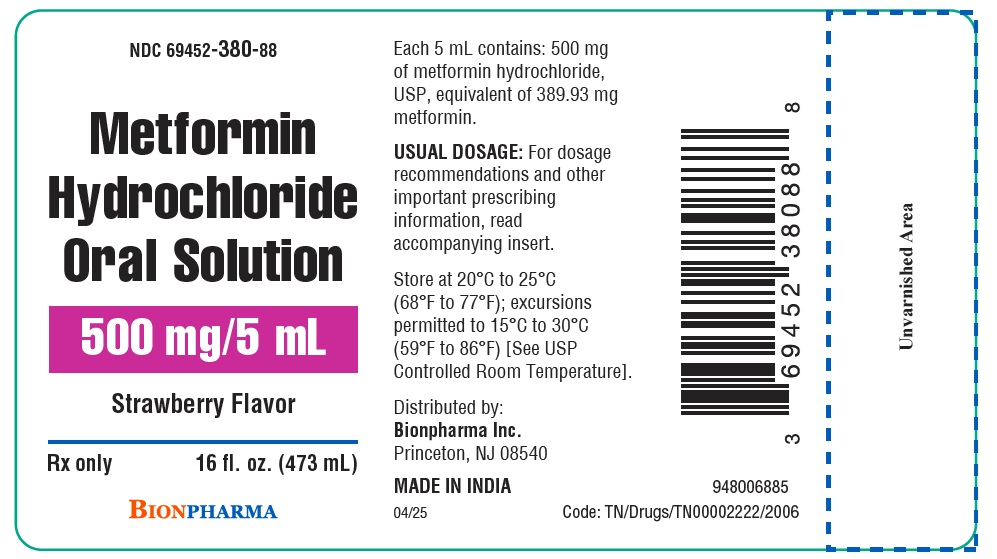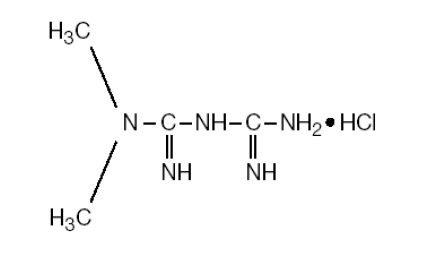 DRUG LABEL: Metformin Hydrochloride Oral Solution
NDC: 69452-380 | Form: SOLUTION
Manufacturer: Bionpharma Inc.,
Category: prescription | Type: HUMAN PRESCRIPTION DRUG LABEL
Date: 20260225

ACTIVE INGREDIENTS: METFORMIN HYDROCHLORIDE 500 mg/5 mL
INACTIVE INGREDIENTS: BENZOIC ACID; HYDROCHLORIC ACID; POTASSIUM BICARBONATE; WATER; SUCRALOSE; XANTHAN GUM

HIGHLIGHTS OF PRESCRIBING INFORMATION

These highlights do not include all the information needed to use METFORMIN HYDROCHLORIDE ORAL SOLUTION safely and effectively. See full prescribing information for METFORMIN HYDROCHLORIDE ORAL SOLUTION.
METFORMIN HYDROCHLORIDE oral solution
Initial U.S. Approval: 1995

WARNING: LACTIC ACIDOSIS

See full prescribing information for complete boxed warning.

- Postmarketing cases of metformin-associated lactic acidosis have resulted in death, hypothermia, hypotension, and resistant bradyarrhythmias. Symptoms included malaise, myalgias, respiratory distress, somnolence, and abdominal pain. Laboratory abnormalities included elevated blood lactate levels, anion gap acidosis, increased lactate/pyruvate ratio; and metformin plasma levels generally > 5 mcg/mL. (5.1)
- Risk factors include renal impairment, concomitant use of certain drugs, age ≥ 65 years old, radiological studies with contrast, surgery and other procedures, hypoxic states, excessive alcohol intake, and hepatic impairment. Steps to reduce the risk of and manage metformin-associated lactic acidosis in these high-risk groups are provided in the Full Prescribing Information. (5.1)
- If lactic acidosis is suspected, discontinue metformin hydrochloride oral solution and institute general supportive measures in a hospital setting. Prompt hemodialysis is recommended. (5.1)

1 INDICATIONS AND USAGE

Metformin hydrochloride is a biguanide indicated as an adjunct to diet and exercise to improve glycemic control in adults and pediatric patients 10 years of age and older with type 2 diabetes mellitus. (1)

2 DOSAGE AND ADMINISTRATION

Adult Dosage for Metformin Hydrochloride Oral Solution:

- Starting dose: 500 mg (5 mL) orally twice a day or 850 mg (8.5 mL) once a day, with meals (2.1)
- Increase the dose in increments of 500 mg (5 mL) weekly or 850 mg (8.5 mL) every 2 weeks, up to a maximum dose of 2,550 mg (25.5 mL) per day, given in divided doses (2.1)
- Doses above 2,000 mg (20 mL) may be better tolerated given in divided doses 3 times a day with meals (2.1)

Pediatric Dosage for Metformin Hydrochloride Oral Solution:

- Starting dose: 500 mg (5 mL) orally twice a day, with meals (2.2)
- Increase dosage in increments of 500 mg (5 mL) weekly up to a maximum of 2,000 mg (20 mL) per day, given in divided doses twice daily (2.2)

Renal Impairment:

- Prior to initiation, assess renal function with estimated glomerular filtration rate (eGFR) (2.3)
- Do not use in patients with eGFR below 30 mL/minute/1.73 m^2(2.3)
- Initiation is not recommended in patients with eGFR between 30 mL/minute/1.73 m^2to 45 mL/minute/1.73 m^2(2.3)
- Assess risk/benefit of continuing metformin hydrochloride oral solution if eGFR falls below 45 mL/minute/1.73 m^2(2.3)
- Discontinue if eGFR falls below 30 mL/minute/1.73 m^2(2.3)

Discontinuation for Iodinated Contrast Imaging Procedures:

- Metformin hydrochloride oral solution may need to be discontinued at time of, or prior to, iodinated contrast imaging procedures (2.4)

3 DOSAGE FORMS AND STRENGTHS

Oral Solution: 500 mg per 5 mL (100 mg/mL) in strawberry flavor (3)

4 CONTRAINDICATIONS

- Severe renal impairment (eGFR below 30 mL/min/1.73 m^2) (4, 5.1)
- Hypersensitivity to metformin (4)
- Acute or chronic metabolic acidosis, including diabetic ketoacidosis, with or without coma. (4)

5 WARNINGS AND PRECAUTIONS

- Lactic acidosis:See boxed warning. (5.1)
- Vitamin B12deficiency: Metformin may lower vitamin B12levels. Measure hematological parameters annually and vitamin B12at 2-year to 3-year intervals and manage any abnormalities. (5.2)
- Hypoglycemia with Concomitant Use with Insulin and Insulin Secretagogues:Increased risk of hypoglycemia when used in combination with insulin and/or an insulin secretagogue. Lower dose of insulin or insulin secretagogue may be required (5.3)

6 ADVERSE REACTIONS

The most common adverse reactions are diarrhea, nausea/vomiting, flatulence, asthenia, indigestion, abdominal discomfort, and headache. (6.1)

To report SUSPECTED ADVERSE REACTIONS, contact Bionpharma Inc. at 1-888-235-BION or 1-888-235-2466 or FDA at 1-800-FDA-1088 or http://www.fda.gov/medwatch

7 DRUG INTERACTIONS

- Carbonic anhydrase inhibitors may increase risk of lactic acidosis. Consider more frequent monitoring (7)
- Drugs that reduce metformin clearance (such as ranolazine, vandetanib, dolutegravir, and cimetidine) may increase the accumulation of metformin. Consider the benefits and risks of concomitant use (7)
- Alcohol can potentiate the effect of metformin on lactate metabolism. Warn patients against excessive alcohol intake (7)

8 USE IN SPECIFIC POPULATIONS

- Females and Males of Reproductive Potential: Advise premenopausal females of the potential for an unintended pregnancy. (8.3)
- Geriatric Use: Assess renal function more frequently. (8.5)
- Hepatic Impairment: Avoid use in patients with hepatic impairment. (8.7)

FULL PRESCRIBING INFORMATION

WARNING: LACTIC ACIDOSIS

Postmarketing cases of metformin-associated lactic acidosis have resulted in death, hypothermia, hypotension, and resistant bradyarrhythmias. The onset of metformin‑ associated lactic acidosis is often subtle, accompanied only by nonspecific symptoms such as malaise, myalgias, respiratory distress, somnolence, and abdominal pain. Metformin‑ associated lactic acidosis was characterized by elevated blood lactate levels (>5 mmol/Liter), anion gap acidosis (without evidence of ketonuria or ketonemia), an increased lactate/pyruvate ratio; and metformin plasma levels generally > 5 mcg/mL [see Warnings and Precautions (5.1) ].

Risk factors for metformin-associated lactic acidosis include renal impairment, concomitant use of certain drugs (e.g. carbonic anhydrase inhibitors such as topiramate), age 65 years old or greater, having a radiological study with contrast, surgery and other procedures, hypoxic states (e.g., acute congestive heart failure), excessive alcohol intake, and hepatic impairment.

Steps to reduce the risk of and manage metformin-associated lactic acidosis in these high-risk groups are provided [see Dosage and Administration (2.3), Contraindications (4), and Warnings and Precautions (5.1) ].

If metformin-associated lactic acidosis is suspected, immediately discontinue metformin hydrochloride oral solution and institute general supportive measures in a hospital setting. Prompt hemodialysis is recommended [see Warnings and Precautions (5.1) ].

1 INDICATIONS AND USAGE

Metformin hydrochloride oral solution is indicated as an adjunct to diet and exercise to improve glycemic control in adults and pediatric patients 10 years of age and older with type 2 diabetes mellitus.

2 DOSAGE AND ADMINISTRATION

2.1 Adult Dosage

- Measure the metformin hydrochloride oral solution dose in the metformin hydrochloride oral solution specific dosing cup.
- The recommended starting dose of metformin hydrochloride oral solution is 500 mg (5 mL) orally twice a day or 850 mg (8.5 mL) once a day, given with meals.
- Increase the dose in increments of 500 mg (5 mL) weekly or 850 mg (8.5 mL) every 2 weeks on the basis of glycemic control and tolerability, up to a maximum dose of 2,550 mg (25.5 mL) per day, given in divided doses.
- Doses above 2,000 mg (20 mL) may be better tolerated given in divided doses 3 times a day with meals.

2.2 Pediatric Dosage

- Measure the metformin hydrochloride oral solution dose in the metformin hydrochloride oral solution specific dosing cup.
- The recommended starting dose of metformin hydrochloride oral solution for pediatric patients 10 years of age and older is 500 mg (5 mL) orally twice a day, given with meals.
- Increase dosage in increments of 500 mg (5 mL) weekly on the basis of glycemic control and tolerability, up to a maximum of 2,000 mg (20 mL) per day, given in divided doses twice daily.

2.3 Recommendations for Use in Renal Impairment

- Assess renal function prior to initiation of metformin hydrochloride oral solution and periodically thereafter.
- Metformin hydrochloride oral solution is contraindicated in patients with an estimated glomerular filtration rate (eGFR) below 30 mL/minute/1.73 m^2.
- Initiation of metformin hydrochloride oral solution in patients with an eGFR between 30 mL/minute/1.73 m^2to 45 mL/minute/1.73 m^2is not recommended.
- In patients taking metformin hydrochloride oral solution whose eGFR later falls below 45 mL/min/1.73 m^2, assess the benefit risk of continuing therapy.
- Discontinue metformin hydrochloride oral solution if the patient’s eGFR later falls below 30 mL/minute/1.73 m^2 [see Warnings and Precautions (5.1) ].

2.4 Discontinuation for Iodinated Contrast Imaging Procedures

Discontinue metformin hydrochloride oral solution at the time of, or prior to, an iodinated contrast imaging procedure in patients with an eGFR between 30 mL/minute/1.73 m^2and 60 mL/min/1.73 m^2; in patients with a history of liver disease, alcoholism, or heart failure; or in patients who will be administered intra-arterial iodinated contrast. Re-evaluate eGFR 48 hours after the imaging procedure; restart metformin hydrochloride oral solution if renal function is stable.

3 DOSAGE FORMS AND STRENGTHS

Oral solution: 500 mg per 5 mL (100 mg/mL) clear colorless liquid in strawberry flavor

4 CONTRAINDICATIONS

Metformin hydrochloride oral solution is contraindicated in patients with:

- Severe renal impairment (eGFR below 30 mL/min/1.73 m^2) [see Warnings and Precautions (5.1) ].
- Hypersensitivity to metformin.
- Acute or chronic metabolic acidosis, including diabetic ketoacidosis, with or without coma.

5 WARNINGS AND PRECAUTIONS

5.1 Lactic Acidosis

There have been postmarketing cases of metformin-associated lactic acidosis, including fatal cases. These cases had a subtle onset and were accompanied by nonspecific symptoms such as malaise, myalgias, abdominal pain, respiratory distress, or increased somnolence; however, hypotension and resistant bradyarrhythmias have occurred with severe acidosis. Metformin-associated lactic acidosis was characterized by elevated blood lactate concentrations (> 5 mmol/L), anion gap acidosis (without evidence of ketonuria or ketonemia), and an increased lactate: pyruvate ratio; metformin plasma levels were generally > 5 mcg/mL. Metformin decreases liver uptake of lactate increasing lactate blood levels which may increase the risk of lactic acidosis, especially in patients at risk.

If metformin-associated lactic acidosis is suspected, general supportive measures should be instituted promptly in a hospital setting, along with immediate discontinuation of metformin hydrochloride oral solution. In metformin hydrochloride oral solution-treated patients with a diagnosis or strong suspicion of lactic acidosis, prompt hemodialysis is recommended to correct the acidosis and remove accumulated metformin (metformin hydrochloride is dialyzable with a clearance of up to 170 mL/min under good hemodynamic conditions). Hemodialysis has often resulted in reversal of symptoms and recovery.

Educate patients and their families about the symptoms of lactic acidosis and, if these symptoms occur, instruct them to discontinue metformin hydrochloride oral solution and report these symptoms to their healthcare provider.

For each of the known and possible risk factors for metformin-associated lactic acidosis, recommendations to reduce the risk of and manage metformin-associated lactic acidosis are provided below:

- Renal impairment—The postmarketing metformin-associated lactic acidosis cases primarily occurred in patients with significant renal impairment.

The risk of metformin accumulation and metformin-associated lactic acidosis increases with the severity of renal impairment because metformin is substantially excreted by the kidney. Clinical recommendations based upon the patient’s renal function include [see Dosage and Administration (2.3), and Clinical Pharmacology (12.3) ]:

- Before initiating metformin hydrochloride oral solution, obtain an estimated glomerular filtration rate (eGFR).
- Metformin hydrochloride oral solution is contraindicated in patients with an eGFR less than 30 mL/min/1.73 m^2 [see Contraindications (4) ].
- Initiation of metformin hydrochloride oral solution is not recommended in patients with eGFR between 30 mL/min/1.73 m^2to 45 mL/min/1.73 m^2.
- Obtain an eGFR at least annually in all patients taking metformin hydrochloride oral solution. In patients at risk for the development of renal impairment (e.g., the elderly), renal function should be assessed more frequently.
- In patients taking metformin hydrochloride oral solution whose eGFR falls below 45 mL/min/1.73 m^2, assess the benefit and risk of continuing therapy.
- Drug interactions— The concomitant use of metformin hydrochloride oral solution with specific drugs may increase the risk of metformin-associated lactic acidosis: those that impair renal function, result in significant hemodynamic change, interfere with acid-base balance, or increase metformin accumulation. Consider more frequent monitoring of patients [see Drug Interactions (7)] .
- Age 65 or greater— The risk of metformin-associated lactic acidosis increases with the patient’s age because elderly patients have a greater likelihood of having hepatic, renal, or cardiac impairment than younger patients. Assess renal function more frequently in elderly patients.
- Radiologic studies with contrast —Administration of intravascular iodinated contrast agents in metformin-treated patients has led to an acute decrease in renal function and the occurrence of lactic acidosis. Stop metformin hydrochloride oral solution at the time of, or prior to, an iodinated contrast imaging procedure in patients with an eGFR between 30 mL/min/1.73 m^2and 60 mL/min/1.73 m^2; in patients with a history of hepatic impairment, alcoholism or heart failure; or in patients who will be administered intra- arterial iodinated contrast. Re-evaluate eGFR 48 hours after the imaging procedure, and restart metformin hydrochloride oral solution if renal function is stable.
- Surgery and other procedures —Withholding of food and fluids during surgical or other procedures may increase the risk for volume depletion, hypotension, and renal impairment. Metformin hydrochloride oral solution should be temporarily discontinued while patients have restricted food and fluid intake.
- Hypoxic states —Several of the postmarketing cases of metformin-associated lactic acidosis occurred in the setting of acute congestive heart failure (particularly when accompanied by hypoperfusion and hypoxemia). Cardiovascular collapse (shock), acute myocardial infarction, sepsis, and other conditions associated with hypoxemia have been associated with lactic acidosis and may cause prerenal azotemia. When such an event occurs, discontinue metformin hydrochloride oral solution.
- Excessive alcohol intake —Alcohol potentiates the effect of metformin on lactate metabolism. Patients should be warned against excessive alcohol intake while receiving metformin hydrochloride oral solution.
- Hepatic impairment —Patients with hepatic impairment have developed cases of metformin- associated lactic acidosis. This may be due to impaired lactate clearance resulting in higher lactate blood levels. Therefore, avoid use of metformin hydrochloride oral solution in patients with clinical or laboratory evidence of hepatic disease.

5.2 Vitamin B12Deficiency

In clinical trials of 29-week duration with metformin hydrochloride (HCl) tablets, a decrease to subnormal levels of previously normal serum vitamin B12levels was observed in approximately 7% of patients. Such decrease, possibly due to interference with B12absorption from the B12-intrinsic factor complex, may be associated with anemia but appears to be rapidly reversible with discontinuation of metformin or vitamin B12supplementation. Certain individuals (those with inadequate vitamin B12or calcium intake or absorption) appear to be predisposed to developing subnormal vitamin B12levels. Measure hematologic parameters on an annual basis and vitamin B12at 2-year to 3-year intervals in patients on metformin hydrochloride oral solution and manage any abnormalities [see Adverse Reactions (6.1) ].

5.3 Hypoglycemia with Concomitant Use with Insulin and Insulin Secretagogues

Insulin and insulin secretagogues (e.g., sulfonylurea) are known to cause hypoglycemia. Metformin hydrochloride oral solution may increase the risk of hypoglycemia when combined with insulin and/or an insulin secretagogue. Therefore, a lower dose of insulin or insulin secretagogue may be required to minimize the risk of hypoglycemia when used in combination with metformin hydrochloride oral solution [see Drug Interactions (7)].

5.4 Macrovascular Outcomes

There have been no clinical studies establishing conclusive evidence of macrovascular risk reduction with metformin hydrochloride oral solution.

6 ADVERSE REACTIONS

- The following adverse reactions are also discussed elsewhere in the labeling:
- Lactic Acidosis [see Boxed Warning and Warningsand Precautions (5.1)]
- Vitamin B12Deficiency [see Warnings and Precautions (5.2) ]
- Hypoglycemia [see Warnings and Precautions (5.3)]

6.1 Clinical Studies Experience

Because clinical trials are conducted under widely varying conditions, adverse reaction rates observed in the clinical trials of a drug cannot be directly compared to rates in the clinical trials of another drug and may not reflect the rates observed in practice.

In a U.S. clinical trial of metformin HCl tablets in patients with type 2 diabetes mellitus, a total of 141 patients received metformin HCl tablets up to 2,550 mg per day. Adverse reactions reported in greater than 5% of patients treated with metformin HCl tablets and that were more common than in placebo-treated patients, are listed in Table 1.

Table 1: Adverse Reactions from a Clinical Trial of Metformin HCl Tablets Occurring > 5% and More Common than Placebo in Patients with Type 2 Diabetes Mellitus
 | Metformin HCl Tablets (n = 141) | Placebo (n = 145)
Diarrhea | 53% | 12%
Nausea/Vomiting | 26% | 8%
Flatulence | 12% | 6%
Asthenia | 9% | 6%
Indigestion | 7% | 4%
Abdominal Discomfort | 6% | 5%
Headache | 6% | 5%

Diarrhea led to discontinuation of metformin HCl tablets in 6% of patients. Additionally, the following adverse reactions were reported in ≥ 1% to ≤ 5% of patients treated with metformin HCl tablets and were more commonly reported than placebo: abnormal stools, hypoglycemia, myalgia, lightheaded, dyspnea, nail disorder, rash, sweating increased, taste disorder, chest discomfort, chills, flu syndrome, flushing, palpitation.

Pediatric Patients

In clinical trials with metformin HCl tablets in pediatric patients with type 2 diabetes mellitus, the profile of adverse reactions was similar to that observed in adults.

Laboratory Tests

Vitamin B12Concentrations

In clinical trials of 29-week duration with metformin HCl tablets, a decrease to subnormal levels of previously normal serum vitamin B12levels was observed in approximately 7% of patients.

6.2 Postmarketing Experience

The following adverse reactions have been identified during post approval use of metformin. Because these reactions are reported voluntarily from a population of uncertain size, it is not always possible to reliably estimate their frequency or establish a causal relationship to drug exposure.

Cholestatic, hepatocellular, and mixed hepatocellular liver injury have been reported with postmarketing use of metformin.

7 DRUG INTERACTIONS

Table 2 presents clinically significant drug interactions with metformin hydrochloride oral solution.

Table 2: Clinically Significant Drug Interactions with Metformin Hydrochloride Oral Solution

Carbonic Anhydrase Inhibitors
Clinical Impact: | Carbonic anhydrase inhibitors frequently cause a decrease in serum bicarbonate and induce non-anion gap, hyperchloremic metabolic acidosis. Concomitant use of these drugs with metformin hydrochloride oral solution may increase the risk for lactic acidosis.
Intervention: | Consider more frequent monitoring of these patients.
Examples: | Topiramate, zonisamide, acetazolamide or dichlorphenamide.
Drugs that Reduce Metformin Hydrochloride Oral Solution Clearance
Clinical Impact: | Concomitant use of drugs that interfere with common renal tubular transport systems involved in the renal elimination of metformin (e.g., organic cationic transporter-2 [OCT2]/ multidrug and toxin extrusion [MATE] inhibitors) could increase systemic exposure to metformin and may increase the risk for lactic acidosis [see Clinical Pharmacology (12.3)] .
Intervention: | Consider the benefits and risks of concomitant use with metformin hydrochloride oral solution.
Examples: | Ranolazine, vandetanib, dolutegravir, and cimetidine.
Alcohol
Clinical Impact: | Alcohol is known to potentiate the effect of metformin on lactate metabolism.
Intervention: | Warn patients against excessive alcohol intake while receiving metformin hydrochloride oral solution.
Insulin Secretagogues or Insulin
Clinical Impact: | Co-administration of metformin hydrochloride oral solution with an insulin secretagogue (e.g., sulfonylurea) or insulin may increase the risk of hypoglycemia.
Intervention: | Patients receiving an insulin secretagogue or insulin may require lower doses of the insulin secretagogue or insulin.
Drugs Affecting Glycemic Control
Clinical Impact: | Certain drugs tend to produce hyperglycemia and may lead to loss of glycemic control.
Intervention: | When such drugs are administered to a patient receiving metformin hydrochloride oral solution, observe the patient closely for loss of blood glucose control. When such drugs are withdrawn from a patient receiving metformin hydrochloride oral solution, observe the patient closely for hypoglycemia.
Examples: | Thiazides and other diuretics, corticosteroids, phenothiazines, thyroid products, estrogens, oral contraceptives, phenytoin, nicotinic acid, sympathomimetics, calcium channel blockers, and isoniazid.

8 USE IN SPECIFIC POPULATIONS

8.1 Pregnancy

Risk Summary

Limited data with metformin hydrochloride oral solution in pregnant women are not sufficient to determine a drug-associated risk for major birth defects or miscarriage. Published studies with metformin use during pregnancy have not reported a clear association with metformin and major birth defect or miscarriage risk [see Data]. There are risks to the mother and fetus associated with poorly controlled diabetes mellitus in pregnancy [see Clinical Considerations].

No adverse developmental effects were observed when metformin was administered to pregnant Sprague Dawley rats and rabbits during the period of organogenesis at doses up to 2-times and 5-times, respectively, a 2,550 mg clinical dose, based on body surface area [see Data].

The estimated background risk of major birth defects is 6% to 10% in women with pre-gestational diabetes mellitus with an HbA1C >7 and has been reported to be as high as 20% to 25% in women with a HbA1C >10. The estimated background risk of miscarriage for the indicated population is unknown. In the U.S. general population, the estimated background risk of major birth defects and miscarriage in clinically recognized pregnancies is 2% to 4% and 15% to 20%, respectively.

Clinical Considerations

Disease-associated maternal and/or embryo/fetal risk

Poorly-controlled diabetes mellitus in pregnancy increases the maternal risk for diabetic ketoacidosis, pre-eclampsia, spontaneous abortions, preterm delivery, stillbirth and delivery complications. Poorly controlled diabetes mellitus increases the fetal risk for major birth defects, stillbirth, and macrosomia related morbidity.

Data

Human Data

Published data from post-marketing studies have not reported a clear association with metformin and major birth defects, miscarriage, or adverse maternal or fetal outcomes when metformin was used during pregnancy. However, these studies cannot definitely establish the absence of any metformin- associated risk because of methodological limitations, including small sample size and inconsistent comparator groups.

Animal Data

Metformin hydrochloride did not adversely affect development outcomes when administered to pregnant rats and rabbits at doses up to 600 mg/kg/day. This represents an exposure of about 2 times and 5 times a 2,550 mg clinical dose based on body surface area comparisons for rats and rabbits, respectively. Determination of fetal concentrations demonstrated a partial placental barrier to metformin.

8.2 Lactation

Risk Summary

Limited published studies report that metformin is present in human milk [see Data]. However, there is insufficient information to determine the effects of metformin on the breastfed infant and no available information on the effects of metformin on milk production. Therefore, the developmental and health benefits of breastfeeding should be considered along with the mother’s clinical need for metformin hydrochloride oral solution and any potential adverse effects on the breastfed child from metformin hydrochloride oral solution or from the underlying maternal condition.

Data

Published clinical lactation studies report that metformin is present in human milk which resulted in infant doses approximately 0.11% to 1% of the maternal weight-adjusted dosage and a milk/plasma ratio ranging between 0.13 and 1. However, the studies were not designed to definitely establish the risk of use of metformin during lactation because of small sample size and limited adverse event data collected in infants.

8.3 Females and Males of Reproductive Potential

Discuss the potential for unintended pregnancy with premenopausal women as therapy with metformin hydrochloride oral solution may result in ovulation in some anovulatory women.

8.4 Pediatric Use

The safety and effectiveness of metformin hydrochloride oral solution for the treatment of type 2 diabetes mellitus have been established in pediatric patients 10 years to 16 years old. Safety and effectiveness of metformin hydrochloride oral solution have not been established in pediatric patients less than 10 years old.

Use of metformin hydrochloride oral solution in pediatric patients 10 years to 16 years old for the treatment of type 2 diabetes mellitus is supported by evidence from adequate and well-controlled studies of metformin HCl tablets in adults with additional data from a controlled clinical study of metformin HCl tablets in pediatric patients 10 years to 16 years old with type 2 diabetes mellitus, which demonstrated a similar response in glycemic control to that seen in adults [see Clinical Studies (14)] . In this study, adverse reactions were similar to those described in adults. A maximum daily dose of 2,000 mg of metformin hydrochloride oral solution is recommended [See Dosage and Administration (2.2) ].

8.5 Geriatric Use

Controlled clinical studies of metformin HCl tablets did not include sufficient numbers of elderly patients to determine whether they respond differently from younger patients. In general, dose selection for an elderly patient should be cautious, usually starting at the low end of the dosing range, reflecting the greater frequency of decreased hepatic, renal, or cardiac function, and of concomitant disease or other drug therapy and the higher risk of lactic acidosis. Assess renal function more frequently in elderly patients [see Warnings and Precautions (5.1) ].

8.6 Renal Impairment

Metformin is substantially excreted by the kidney, and the risk of metformin accumulation and lactic acidosis increases with the degree of renal impairment. Metformin hydrochloride oral solution is contraindicated in severe renal impairment, patients with an estimated glomerular filtration rate (eGFR) below 30 mL/min/1.73 m^2 [see Dosage and Administration (2.3), Contraindications (4), Warnings and Precautions (5.1), and Clinical Pharmacology (12.3) ].

8.7 Hepatic Impairment

Use of metformin in patients with hepatic impairment has been associated with some cases of lactic acidosis. Metformin hydrochloride oral solution is not recommended in patients with hepatic impairment [see Warnings and Precautions (5.1) ].

10 OVERDOSAGE

Overdose of metformin hydrochloride has occurred, including ingestion of amounts greater than 50 grams. Hypoglycemia was reported in approximately 10% of cases, but no causal association with metformin has been established. Lactic acidosis has been reported in approximately 32% of metformin overdose cases [see Warnings and Precautions (5.1) ]. Metformin is dialyzable with a clearance of up to 170 mL/min under good hemodynamic conditions. Therefore, hemodialysis may be useful for removal of accumulated drug from patients in whom metformin overdosage is suspected.

11 DESCRIPTION

Metformin hydrochloride oral solution contains the biguanidine antihyperglycemic agent metformin in the form of monohydrochloride salt. Metformin hydrochloride, USP is N,N-dimethylimidodicarbonimidic diamide hydrochloride. The structural formula is shown as:

Metformin hydrochloride, USP is a white crystalline powder with a molecular formula of C4H11N5•HCl and a molecular weight of 165.6 g/mol. The pKa of metformin is 2.8, 11.5 (32 ºC). The pH of a 10% aqueous solution of metformin hydrochloride is 6.89. It is freely soluble in purified water; slightly soluble in alcohol; practically insoluble in acetone and in methylene chloride.

Metformin hydrochloride oral solution contains 500 mg of metformin hydrochloride, USP (the equivalent of 389.93 mg metformin) per 5 mL and the following inactive ingredients: Benzoic acid, hydrochloric acid, potassium bicarbonate, purified water, strawberry flavor, sucralose, and xanthan gum.

12 CLINICAL PHARMACOLOGY

12.1 Mechanism of Action

Metformin is an antihyperglycemic agent which improves glucose tolerance in patients with type 2 diabetes mellitus, lowering both basal and postprandial plasma glucose. Metformin decreases hepatic glucose production, decreases intestinal absorption of glucose, and improves insulin sensitivity by increasing peripheral glucose uptake and utilization. With metformin therapy, insulin secretion remains unchanged while fasting insulin levels and day-long plasma insulin response may decrease.

12.3 Pharmacokinetics

Absorption

Two pharmacokinetic studies performed in healthy volunteers to evaluate the bioavailability of metformin hydrochloride oral solution in comparison with metformin HCl tablets under fasting and fed conditions showed that the rate and extent of absorption of metformin hydrochloride oral solution was found to be comparable to that of metformin HCl tablets under fasting or fed conditions (see Table 3).

Table 3: Select Mean (± S.D.) Pharmacokinetic Parameters Following Single Oral Doses of 1,000 mg Metformin Hydrochloride Oral Solution and Metformin HCl Tablets in healthy, nondiabetic adults (n = 36) under fed and fasting conditions
Formulation | Cmax(ng/mL) | AUC0-(ng.h/mL) | Tmax(h)
Study 1- Fasting state
Metformin Hydrochloride Oral Solution | 1,540.1 ± 451.1 | 9,069.6 ± 2,593.6 | 2.2 ± 0.5
Metformin HCl Tablets | 1,885.1 ± 498.5 | 11,100.1 ± 2,733.1 | 2.5 ± 0.6
T/R Ratio X 100 (90% confidence interval) | 81.2; (76.3 to 86.4) | 81.2; (76.9 to 85.6) | -
Study 2- Fed State
Metformin Hydrochloride Oral Solution | 1,235.3 ± 177.7 | 8,950.1 ± 1,381.2 | 4.1 ± 0.8
Metformin HCl Tablets | 1,361 ± 298.8 | 9,307.7 ± 1,839.8 | 3.7 ± 0.8
T/R Ratio X 100 (90% confidence interval) | 91.8; (87.4 to 96.5) | 97.0; (92.9 to 101.2) | -

T-test product (Metformin hydrochloride oral solution)
R-reference product (immediate release metformin HCl tablets)

Studies using single oral doses of metformin HCl tablets 500 mg to 1,500 mg, and 850 mg to 2,550 mg, indicate that there is a lack of dose proportionality with increasing doses, which is due to decreased absorption rather than an alteration in elimination. At usual clinical doses and dosing schedules of metformin, steady state plasma concentrations of metformin are reached within 24 hours to 48 hours and are generally < 1 mcg/mL.

Effect of food:The food-effect study assessed the effects of a high fat/high calorie meal and a low fat/low calorie meal on the bioavailability of metformin hydrochloride oral solution in comparison with administration in the fasted state, in healthy volunteers. The extent of absorption was increased by approximately 16% and 13% with the low fat/low calorie meal and the high fat/high calorie meal, respectively, compared with the administration in the fasted state. The rate and extent of absorption with high fat/high calorie and low fat/ low calorie meal were similar. The mean tmaxwas 2.5 hours under fasting conditions as compared to 3.9 hours with both low fat/ low calorie meal and high fat/high calorie meals (see Table 4).

Table 4: Select Mean (± S.D.) Metformin Pharmacokinetic Parameters Following Single Oral Doses of 1,000 mg Metformin Hydrochloride Oral Solution in healthy, nondiabetic adults (n = 33) under fed (high fat/high calorie meal and low fat/low calorie meal) and fasting conditions (study 3)
Meal type | Cmax; (ng/mL) | AUC0-; (ng.h/mL) | tmax; (h)
Fasting (F) | 1,641.5 ± 551.8 | 9,982.9 ± 2,544.5 | 2.5 ± 0.9
Low fat/ low calorie meal (L) | 1,525.8 ± 396.7 | 11,542.0 ± 2,947.5 | 3.9 ± 0.6
High fat/high calorie meal (H) | 1,432.5 ± 346.8 | 11,184.5 ± 2,446.1 | 3.9 ± 0.8
L/F Ratio X 100 (90% confidence interval) | 94.6; (84.0 to 106.5) | 115.6; (103.6 to 128.9) | -
H/F Ratio X 100 (90% confidence interval) | 89.4; (79.4 to 100.6) | 112.6; (100.9 to 125.6) | -
L/H Ratio X 100 (90% confidence interval) | 105.8; (94.0 to 119.2) | 102.7; (92.0 to 114.6) | -

Distribution

The apparent volume of distribution (V/F) of metformin following single oral doses of metformin HCl 850 mg averaged 654 L ± 358 L. Metformin is negligibly bound to plasma proteins. Metformin partitions into erythrocytes, most likely as a function of time.

Metabolism

Intravenous single-dose studies in normal subjects demonstrate that metformin is excreted unchanged in the urine and does not undergo hepatic metabolism (no metabolites have been identified in humans) nor biliary excretion.

Elimination

Renal clearance (see Table 5) is approximately 3.5 times greater than creatinine clearance, which indicates that tubular secretion is the major route of metformin elimination. Following oral administration, approximately 90% of the absorbed drug is eliminated via the renal route within the first 24 hours, with a plasma elimination half-life of approximately 6.2 hours. In blood, the elimination half-life is approximately 17.6 hours, suggesting that the erythrocyte mass may be a compartment of distribution.

Specific Populations

Renal Impairment

In patients with decreased renal function the plasma and blood half-life of metformin is prolonged and the renal clearance is decreased (see Table 5) [see Dosage and Administration (2.3), Contraindications (4), Warnings and Precautions (5.1) and Use in Specific Populations (8.6) ].

Hepatic Impairment

No pharmacokinetic studies of metformin have been conducted in patients with hepatic impairment [see Warnings and Precautions (5.1) and Use in Specific Populations (8.7) ].

Geriatrics

Limited data from controlled pharmacokinetic studies of metformin HCl tablets in healthy elderly subjects suggest that total plasma clearance of metformin is decreased, the half-life is prolonged, and Cmax is increased, compared to healthy young subjects. It appears that the change in metformin pharmacokinetics with aging is primarily accounted for by a change in renal function (see Table 5) [see Warnings and Precautions (5.1) and Use in Specific Populations (8.5) ].

Table 5: Select Mean (±S.D.) Metformin Pharmacokinetic Parameters Following Single or Multiple Oral Doses of Metformin HCl Tablets

Subject Groups: Metformin HCl dose [All doses given fasting except the first 18 doses of the multiple dose studies] (number of subjects) | Cmax [Peak plasma concentration]; (mcg/mL) | Tmax [Time to peak plasma concentration]; (hrs) | Renal Clearance; (mL/min)
Healthy, nondiabetic adults:
500 mg single dose (24) | 1.03 (± 0.33) | 2.75 (±0.81) | 600 (±132)
850 mg single dose (74) [Combined results (average means) of five studies: mean age 32 years (range 23 years to 59 years)] | 1.60 (±0.38) | 2.64 (±0.82) | 552 (±139)
850 mg three times daily for 19 doses [Kinetic study done following dose 19, given fasting] (9) | 2.01 (±0.42) | 1.79 (±0.94) | 642 (±173)
Adults with type 2 diabetes mellitus:
850 mg single dose (23) | 1.48 (±0.5) | 3.32 (±1.08) | 491 (±138)
850 mg three times daily for 19 doses¶ (9) | 1.90 (±0.62) | 2.01 (±1.22) | 550 (±160)
Elderly [Elderly subjects, mean age 71 years (range 65 years to 81 years)] , healthy nondiabetic adults:
850 mg single dose (12) | 2.45 (±0.70) | 2.71 (±1.05) | 412 (±98)
Renal-impaired adults:
850 mg single dose Mild(CLcr [CLcr = creatinine clearance normalized to body surface area of 1.73 m 2] 61 mL/min to 90 mL/min) (5) | 1.86 (±0.52) | 3.20 (±0.45) | 384 (±122)
Moderate(CLcr 31mL/min to 60 mL/min) (4) | 4.12 (±1.83) | 3.75 (±0.50) | 108 (±57)
Severe(CLcr 10 mL/min to 30 mL/min) (6) | 3.93 (±0.92) | 4.01 (±1.10) | 130 (±90)

Pediatrics

After administration of a single oral metformin HCl 500 mg tablet with food, geometric mean metformin Cmaxand AUC differed less than 5% between pediatric type 2 diabetic patients (12 years to 16 years of age) and gender- and weight-matched healthy adults (20 years to 45 years of age), all with normal renal function.

Gender
Metformin pharmacokinetic parameters did not differ significantly between normal subjects and patients with type 2 diabetes mellitus when analyzed according to gender (males = 19, females = 16).

Race

No studies of metformin pharmacokinetic parameters according to race have been performed.

Drug Interactions

In Vivo Assessment of Drug Interactions

Table 6: Effect of Co-administered Drug on Plasma Metformin Systemic Exposure

Co-administered Drug | Dose of Co-administered; Drug [All metformin HCl and co-administered drugs were given as single doses] | Dose of Metformin; HCl* | Geometric Mean Ratio (ratio with/without co-administered drug); No Effect = 1.00
Co-administered Drug | Dose of Co-administered; Drug [All metformin HCl and co-administered drugs were given as single doses] | Dose of Metformin; HCl* |  | AUC [AUC = AUC (INF)] | Cmax
No dosing adjustments required for the following:
Glyburide | 5 mg | 850 mg | metformin | 0.91 [Ratio of arithmetic means] | 0.93
Furosemide | 40 mg | 850 mg | metformin | 1.09 | 1.22
Nifedipine | 10 mg | 850 mg | metformin | 1.16 | 1.21
Propranolol | 40 mg | 850 mg | metformin | 0.90 | 0.94
Ibuprofen | 400 mg | 850 mg | metformin | 1.05§ | 1.07§
Cationic drugs eliminated by renal tubular secretion may reduce metformin elimination [see Warnings and Precautions (5.1) and Drug Interactions (7) ].
Cimetidine | 400 mg | 850 mg | metformin | 1.40 | 1.61
Carbonic anhydrase inhibitors may cause metabolic acidosis [see Warnings and Precautions (5.1) and Drug Interactions (7) ].
Topiramate | 100 mg§ | 500 mg§ | metformin | 1.25 [At steady state with topiramate 100 mg every 12 hours and metformin 500 mg every 12 hours; AUC = AUC0-12h] | 1.17

Table 7: Effect of Metformin on Co-administered Drug Systemic Exposure

Co-administered Drug | Dose of Co-administered Drug [All metformin HCl and co-administered drugs were given as single doses] | Dose of Metformin HCl* | Geometric Mean Ratio (ratio with/without metformin); No Effect = 1.00
Co-administered Drug | Dose of Co-administered Drug [All metformin HCl and co-administered drugs were given as single doses] | Dose of Metformin HCl* |  | AUC [AUC = AUCinf unless otherwise noted] | Cmax
No dosing adjustments required for the following:
Glyburide | 5 mg | 850 mg | glyburide | 0.78 [Ratio of arithmetic means, p-value of difference < 0.05] | 0.63
Furosemide | 40 mg | 850 mg | furosemide | 0.87 | 0.69
Nifedipine | 10 mg | 850 mg | nifedipine | 1.10 [AUC0-24 hr reported] | 1.08
Propranolol | 40 mg | 850 mg | propranolol | 1.01§ | 1.02
Ibuprofen | 400 mg | 850 mg | ibuprofen | 0.97 [Ratio of arithmetic means] | 1.01¶
Cimetidine | 400 mg | 850 mg | cimetidine | 0.95§ | 1.01

13 NONCLINICAL TOXICOLOGY

13.1 Carcinogenesis, Mutagenesis, Impairment of Fertility

Long-term carcinogenicity studies have been performed in rats (dosing duration of 104 weeks) and mice (dosing duration of 91 weeks) at doses up to and including 900 mg/kg/day and 1,500 mg/kg/day, respectively. These doses are both approximately 3 times the maximum recommended human daily dose of 2,550 mg based on body surface area comparisons. No evidence of carcinogenicity with metformin was found in either male or female mice. Similarly, there was no tumorigenic potential observed with metformin in male rats. There was, however, an increased incidence of benign stromal uterine polyps in female rats treated with 900 mg/kg/day.

There was no evidence of a mutagenic potential of metformin in the following in vitrotests: Ames test (S. typhimurium), gene mutation test (mouse lymphoma cells), or chromosomal aberrations test (human lymphocytes). Results in the in vivomouse micronucleus test were also negative.

Fertility of male or female rats was unaffected by metformin when administered at doses as high as 600 mg/kg/day, which is approximately 2 times the maximum recommended human daily dose of 2,550 mg based on body surface area comparisons.

14 CLINICAL STUDIES

Adult Clinical Studies

A double-blind, placebo-controlled, multi-center US clinical trial involving obese patients with type 2 diabetes mellitus whose hyperglycemia was not adequately controlled with dietary management alone (baseline fasting plasma glucose [FPG] of approximately 240 mg/dL) was conducted. Patients were treated with metformin HCl tablets (up to 2,550 mg/day) or placebo for 29 weeks. The results are presented in Table 8.

Table 8: Mean Change in Fasting Plasma Glucose and HbA1c at Week 29 Comparing Metformin HCl Tablets vs Placebo in Patients with Type 2 Diabetes Mellitus

 | Metformin HCLTablets; (n = 141) | Placebo; (n = 145) | p-Value
FPG (mg/dL); Baseline; Change at FINAL VISIT | 241.5; -53.0 | 237.7; 6.3 | NS [Not statistically significant]; 0.001
Hemoglobin A1c(%); Baseline; Change at FINAL VISIT | 8.4; -1.4 | 8.2; 0.4 | NS*; 0.001

Mean baseline body weight was 201 lbs and 206 lbs in the metformin HCl tablet and placebo arms, respectively. Mean change in body weight from baseline to week 29 was -1.4 lbs and ‑2.4 lbs in the metformin HCl tablet and placebo arms, respectively.

A 29-week, double-blind, placebo-controlled study of metformin HCl tablet and glyburide, alone and in combination, was conducted in obese patients with type 2 diabetes mellitus who had failed to achieve adequate glycemic control while on maximum doses of glyburide (baseline FPG of approximately 250 mg/dL). Patients randomized to the combination arm started therapy with metformin HCl tablet 500 mg and glyburide 20 mg. At the end of each week of the first 4 weeks of the trial, these patients had their dosages of metformin HCl increased by 500 mg if they had failed to reach target fasting plasma glucose. After week 4, such dosage adjustments were made monthly, although no patient was allowed to exceed metformin HCl 2,500 mg. Patients in the metformin only arm (metformin HCl plus placebo) discontinued glyburide and followed the same titration schedule. Patients in the glyburide arm continued the same dose of glyburide. At the end of the trial, approximately 70% of the patients in the combination group were taking metformin HCl 2,000 mg/glyburide 20 mg or metformin HCl 2,500 mg/glyburide 20 mg. The results are displayed in Table 9.

Table 9: Mean Change in Fasting Plasma Glucose and HbA1c at Week 29 Comparing Metformin HCl Tablets/Glyburide (Comb) vs Glyburide (Glyb) vs Metformin HCl Tablets (GLU): in Patients with Type 2 Diabetes Mellitus with Inadequate Glycemic Control on Glyburide

 | Comb; (n = 213) | Glyb; (n = 209) | GLU; (n = 210) | p-Values
 | Comb; (n = 213) | Glyb; (n = 209) | GLU; (n = 210) | Glyb; vs; Comb | GLU; vs; Comb | GLU; vs; Glyb
Fasting Plasma Glucose (mg/dL); Baseline; Change at FINAL VISIT | 250.5; -63.5 | 247.5; 13.7 | 253.9; -0.9 | NS [Not statistically significant]; 0.001 | NS*; 0.001 | NS*; 0.025
Hemoglobin A1c(%); Baseline; Change at FINAL VISIT | 8.8; -1.7 | 8.5; 0.2 | 8.9; -0.4 | NS*; 0.001 | NS*; 0.001 | 0.007*; 0.001

Mean baseline body weight was 202 lbs, 203 lbs, and 204 lbs in the metformin HCl tablet/glyburide, glyburide, and metformin HCl tablet arms, respectively. Mean change in body weight from baseline to week 29 was 0.9 lbs, -0.7 lbs, and -8.4 lbs in the metformin HCl tablet/glyburide, glyburide, and metformin HCl tablet arms, respectively.

Pediatric Clinical Studies

A double-blind, placebo-controlled study was conducted in pediatric patients aged 10 to 16 years with type 2 diabetes mellitus (mean FPG 182.2 mg/dL), where patients were treated with metformin HCl tablets (up to 2,000 mg/day) for up to 16 weeks (mean duration of treatment 11 weeks). The results are displayed in Table 10.

Table 10: Mean Change in Fasting Plasma Glucose at Week 16 Comparing Metformin HCl Tablets vs Placebo in Pediatric Patients [Pediatric patients mean age 13.8 years (range 10 years to16 years)] with Type 2 Diabetes Mellitus
 | Metformin HCl Tablets | Placebo | p-Value
FPG (mg/dL); Baseline; Change at FINAL VISIT | (n = 37); 162.4; 42.9 | (n = 36); 192.3; 21.4 | <0.001

Mean baseline body weight was 205 lbs and 189 lbs in the metformin HCl tablet and placebo arms, respectively. Mean change in body weight from baseline to week 16 was -3.3 lbs and -2.0 lbs in the metformin HCl tablet and placebo arms, respectively.

16 HOW SUPPLIED/STORAGE AND HANDLING

How Supplied

Metformin hydrochloride oral solution 500 mg per 5 mL (100 mg per mL) is supplied in bottles with child-resistant caps and a dosing cup as follows:

Flavor | Appearance | Size | NDC
Strawberry | clear, colorless liquid | 4 ounce (118 mL) | 69452-380-55
Strawberry | clear, colorless liquid | 16 ounce (473 mL) | 69452-380-88

Storage

Store at 20°C to 25°C (68°F to 77°F); excursions permitted to 15°C to 30°C (59°F to 86°F) [See USP Controlled Room Temperature].

17 PATIENT COUNSELING INFORMATION

Advise the patient to read the FDA-approved patient labeling (Patient Information).

Administration

Instruct patients or caregivers to use the supplied dosing cup to measure the prescribed amount of medication. Inform patients that additional metformin hydrochloride oral solution dosing cups or oral dosing syringes may be obtained from their pharmacy.

Lactic Acidosis

Explain the risks of lactic acidosis, its symptoms, and conditions that predispose to its development. Advise patients to discontinue metformin hydrochloride oral solution immediately and to promptly notify their healthcare provider if unexplained hyperventilation, myalgias, malaise, unusual somnolence or other nonspecific symptoms occur. Counsel patients against excessive alcohol intake and inform patients about importance of regular testing of renal function while receiving metformin hydrochloride oral solution. Instruct patients to inform their doctor that they are taking metformin hydrochloride oral solution prior to any surgical or radiological procedure, as temporary discontinuation may be required [see Warnings and Precautions (5.1)] .

Hypoglycemia

Inform patients that hypoglycemia may occur when metformin hydrochloride oral solution is co-administered with oral sulfonylureas and insulin. Explain to patients receiving concomitant therapy the risks of hypoglycemia, its symptoms and treatment, and conditions that predispose to its development [see Warnings and Precautions (5.3)] .

Vitamin B12Deficiency

Inform patients about importance of regular hematological parameters while receiving metformin hydrochloride oral solution [see Warnings and Precautions (5.2)] .

Females of Reproductive Age

Inform females that treatment with metformin hydrochloride oral solution may result in ovulation in some premenopausal anovulatory women which may lead to unintended pregnancy [see Use in Specific Populations (8.3)] .

Distributed by: Bionpharma Inc.

Princeton, NJ 08540
MADE IN INDIA

Revised: 08/2025
FDA-03

948026889

PATIENT INFORMATION

Metformin Hydrochloride (met for’ min hye”droe klor’ ide)

Oral Solution

What is the most important information I should know about metformin hydrochloride oral solution?

Metformin hydrochloride oral solution can cause serious side effects, including:

Lactic Acidosis. Metformin hydrochloride, the medicine in metformin hydrochloride oral solution, can cause a rare, but serious side effect called lactic acidosis (a build-up of lactic acid in the blood) that can cause death. Lactic acidosis is a medical emergency and must be treated in a hospital.

Stop taking metformin hydrochloride oral solution and call your healthcare provider right away if you get any of the following symptoms of lactic acidosis:

- feel very weak and tired

- have unusual sleepiness or sleep longer than usual

- have unusual (not normal) muscle pain

- feel cold, especially in your arms and legs

- have trouble breathing

- feel dizzy or lightheaded

- have unexplained stomach or intestinal problems with nausea and vomiting, or diarrhea

- have a slow or irregular heartbeat

You have a higher chance of getting lactic acidosis if you:

- have moderate to severe kidney problems. See “ Do not take metformin hydrochloride oral solution if you”.
- have liver problems.
- have congestive heart failure that requires treatment with medicines.
- drink a lot of alcohol (very often or short-term “binge” drinking).
- get dehydrated (lose a large amount of body fluids). This can happen if you are sick with a fever, vomiting, or diarrhea. Dehydration can also happen when you sweat a lot with activity or exercise and do not drink enough fluids.
- have certain x-ray tests with injectable dyes or contrast agents.
- have surgery.
- have a heart attack, severe infection, or stroke.
- are 65 years of age or older.

Tell your healthcare provider if you have any of the problems in the list above.

Tell your healthcare provider that you are taking metformin hydrochloride oral solution before you have surgery or x-ray tests. Your healthcare provider may need to stop metformin hydrochloride oral solution for a while if you have surgery or certain x-ray tests.

Metformin hydrochloride oral solution can have other serious side effects. See “ What are the possible side effects of metformin hydrochloride oral solution?”.

What is metformin hydrochloride oral solution?

- Metformin hydrochloride oral solution is a prescription medicine that contains metformin hydrochloride. Metformin hydrochloride oral solution is used with diet and exercise to help control high blood sugar (hyperglycemia) in adults and children 10 years of age and older with type 2 diabetes.
- It is not known if metformin hydrochloride oral solution is safe and effective in children under 10 years of age.

Do not take metformin hydrochloride oral solution if you:

- have severe kidney problems.
- are allergic to the metformin hydrochloride or any of the ingredients in metformin hydrochloride oral solution. See the end of this Patient Information leaflet for a complete list of ingredients in metformin hydrochloride oral solution.
- have a condition called metabolic acidosis including diabetic ketoacidosis (high levels of certain acids called “ketones” in your blood or urine).

Before taking metformin hydrochloride oral solution tell your healthcare provider about all your medical conditions, including if you:

- have a history or risk for diabetic ketoacidosis. See “ Do not take metformin hydrochloride oral solution if you?”.
- have kidney problems.
- have liver problems.
- have heart problems, including congestive heart failure.
- are 65 years or older.
- drink alcohol very often or drink a lot of alcohol in short-term “binge” drinking.
- are taking insulin or a sulfonylurea medicine.
- are pregnant or plan to become pregnant. It is not known if metformin hydrochloride oral solution will harm your unborn baby. If you are pregnant, talk with your healthcare provider about the best way to control your blood sugar while you are pregnant.
- are a premenopausal woman who does not have periods regularly or at all. Metformin hydrochloride oral solution can cause the release of an egg from an ovary in a woman (ovulation). This can increase your chance of getting pregnant.
- are breastfeeding or plan to breastfeed. Metformin can pass into your breast milk. Talk with your healthcare provider about the best way to feed your baby while you take metformin hydrochloride oral solution.

Tell your healthcare provider about all the medicines you take, including prescription and over-the-counter medicines, vitamins, and herbal supplements. Know the medicines you take. Keep a list of them to show your healthcare provider and pharmacist when you get a new medicine.

Metformin hydrochloride oral solution may affect the way other medicines work, and other medicines may affect how metformin hydrochloride oral solution works.

How should I take metformin hydrochloride oral solution?

- Take metformin hydrochloride oral solution exactly as your healthcare provider tells you.
- Use the metformin hydrochloride oral solution dosing cup to measure your dose. Ask your pharmacist for a dosing cup if you do not have one.
- Metformin hydrochloride oral solution should be taken with meals to help decrease an upset stomach.
- When your body is under some types of stress, such as fever, trauma (such as a car accident), infection, or surgery, the amount of diabetes medicine that you need may change. Tell your healthcare provider right away if you have any of these problems.
- Your healthcare provider should do blood tests to check how well your kidneys are working before and during your treatment with metformin hydrochloride oral solution.
- Your healthcare provider will check your diabetes with regular blood tests, including your blood sugar levels and your hemoglobin A1C.
- Low blood sugar (hypoglycemia) can happen more often when metformin hydrochloride oral solution is taken with certain other diabetes medicines. Talk to your healthcare provider about how to prevent, recognize and manage low blood sugar. See “What are the possible side effects of metformin hydrochloride oral solution?”.
- Check your blood sugar as your healthcare provider tells you to.
- Stay on your prescribed diet and exercise program while taking metformin hydrochloride oral solution.

If you take too much metformin hydrochloride oral solution, call your healthcare provider, or go to the nearest hospital emergency room right away.

What should I avoid while taking metformin hydrochloride oral solution?

Do not drink a lot of alcoholic drinks while taking metformin hydrochloride oral solution. This means you should not binge drink for short periods, and you should not drink a lot of alcohol on a regular basis. Alcohol can increase the chance of getting lactic acidosis.

What are the possible side effects of metformin hydrochloride oral solution?

Metformin hydrochloride oral solution may cause serious side effects, including:

- See “What is the most important information I should know about metformin hydrochloride oral solution?”
- Low vitamin B12(vitamin B12deficiency). Using metformin hydrochloride oral solution may cause a decrease in the amount of vitamin B12in your blood, especially if you have had low vitamin B12levels before. Your healthcare provider may do blood tests to check your vitamin B12levels.
- Low blood sugar (hypoglycemia).If you take metformin hydrochloride oral solution with another medicine that can cause lower blood sugar, such as a sulfonylurea or insulin, your risk of getting low blood sugar is higher. The dose of your sulfonylurea medicine or insulin may need to be lowered while you take metformin hydrochloride oral solution. Signs and symptoms of low blood sugar may include:

- headache

- hunger

- dizziness

- drowsiness

- fast heartbeat

- sweating

- weakness

- confusion

- irritability

- shaking or feeling jittery

Common side effects of metformin hydrochloride oral solution include:

- diarrhea

- indigestion

- nausea and vomiting

- stomach-area (abdominal) discomfort

- gassiness (flatulence)

- headache

- weakness or lack of energy (asthenia)

These are not all the possible side effects of metformin hydrochloride oral solution.

Call your doctor for medical advice about side effects. You may report side effects to FDA at 1-800-FDA-1088.

How should I store metformin hydrochloride oral solution?

• Store at room temperature between 59°F to 86°F (15°C to 30°C). See insert.

• Keep metformin hydrochloride oral solution and all medicines out of the reach of children.

General information about the safe and effective use of metformin hydrochloride oral solution.

Medicines are sometimes prescribed for purposes other than those listed in a Patient Information leaflet. Do not use metformin hydrochloride oral solution for a condition for which it was not prescribed. Do not give metformin hydrochloride oral solution to other people, even if they have the same symptoms that you have. It may harm them.

You can ask your pharmacist or healthcare provider for information about metformin hydrochloride oral solution that is written for health professionals.

What are the ingredients of metformin hydrochloride oral solution?

Active ingredients: metformin hydrochloride, USP.

Inactive ingredients: Benzoic acid, hydrochloric acid, potassium bicarbonate, purified water, strawberry flavor, sucralose, and xanthan gum.

Distributed by:
Bionpharma Inc.
Princeton, NJ 08540
MADE IN INDIA

For more information, call 1-888-235-BION or 1-888-235-2466.

This Patient Information has approved by the U.S. Food and Drug Administration.

Issued: 11/2023 FDA-01

Package/Label Display Panel

NDC 69452-380-88

Metformin Hydrochloride Oral Solution

500 mg/5 mL

Strawberry Flavor

Rx only

16 fl. oz. (473 mL)